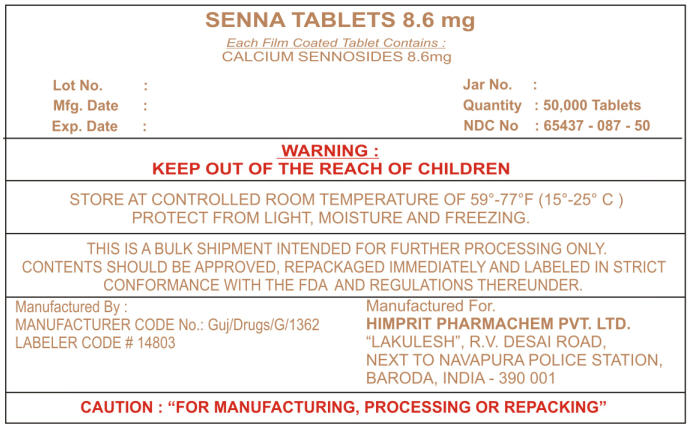 DRUG LABEL: SENNA
NDC: 65437-087 | Form: TABLET, FILM COATED
Manufacturer: HIMPRIT PHARMACHEM PVT LTD
Category: otc | Type: HUMAN OTC DRUG LABEL
Date: 20091111

ACTIVE INGREDIENTS: SENNA 8.6 mg/1 1
INACTIVE INGREDIENTS: MALTODEXTRIN; CELLULOSE, MICROCRYSTALLINE; CROSCARMELLOSE SODIUM; STEARIC ACID; SILICON DIOXIDE; MAGNESIUM STEARATE; HYPROMELLOSE; MINERAL OIL; WATER

SENNA TABLETS 8.6 mg

Drug Facts

Active ingredient (in each tablet)

Sennosides 8.6 mg

Purpose

Laxative

Uses

- relieves occasional constipation (irregularity)
- generally produces a bowel movement in 6-12 hours

Warnings

Do not use

- laxative products for longer than 1 week unless directed by a doctor

Ask a doctor before use if you have

- stomach pain
- nausea
- vomiting
- noticed a sudden change in bowel habits that continues over a period of 2 weeks

Stop use and ask a doctor if you have rectal bleeding or fail to have a bowel movement after use of a laxative. These may indicate a serious condition.

PREGNANCY OR BREAST FEEDING

If pregnant or breast-feeding, ask a health professional before use.

Keep out of reach of children. In case of overdose, get medial help or contact a Poison Control Center right away.

Directions

- take preferably at bedtime or as directed by a doctor

age | starting dosage | maximum dosage
adults and children 12 years of age or older | 2 tablets once a day | 4 tablets twice a day
children 6 to under 12 years | 1 tablet once a day | 2 tablets twice a day
children 2 to under 6 years | 1/2 tablet once a day | 1 tablet twice a day
children under 2 years | ask a doctor | ask a doctor

Other information

- each tablet contains: calcium 25mg
- store at 25°C (77°F); excursions permitted between 15°-30°C (59°-86°F)

Inactive ingredients

croscarmellose sodium, dicalcium phosphate, hypromellose, magnesium stearate, microcrystalline cellulose, mineral oil

PRINCIPAL DISPLAY PANEL - Shipping Label

Each Film Coated Tablet Contains :
CALCIUM SENNOSIDES 8.6mg

Lot No. :
Mfg. Date :
Exp. Date :
Jar No. :
Quantity : 50,000 Tablets
NDC No : 65437 - 087 - 50

WARNING :
KEEP OUT OF THE REACH OF CHILDREN

STORE AT CONTROLLED ROOM TEMPERATURE OF 59°-77°F (15°-25° C)
PROTECT FROM LIGHT, MOISTURE AND FREEZING.

THIS IS A BULK SHIPMENT INTENDED FOR FURTHER PROCESSING ONLY.
CONTENTS SHOULD BE APPROVED, REPACKAGED IMMEDIATELY AND LABELED IN STRICT
CONFORMANCE WITH THE FDA AND REGULATIONS THEREUNDER.

Manufactured By :
MANUFACTURER CODE No.: Guj/Drugs/G/1362
LABELER CODE # 14803

Manufactured For.
HIMPRIT PHARMACHEM PVT. LTD.
"LAKULESH", R.V. DESAI ROAD,
NEXT TO NAVAPURA POLICE STATION,
BARODA, INDIA - 390 001

CAUTION : "FOR MANUFACTURING, PROCESSING OR REPACKING"